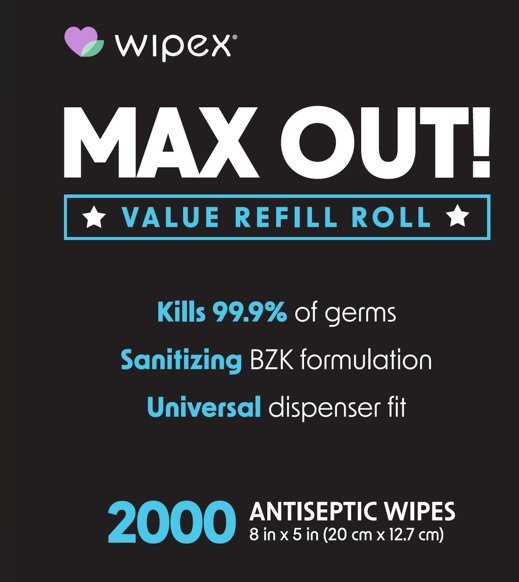 DRUG LABEL: Max OUT
NDC: 74680-221 | Form: CLOTH
Manufacturer: Unico
Category: otc | Type: HUMAN OTC DRUG LABEL
Date: 20260101

ACTIVE INGREDIENTS: BENZALKONIUM CHLORIDE 1.3 mg/1 mL
INACTIVE INGREDIENTS: POTASSIUM SORBATE; SODIUM CHLORIDE; CITRIC ACID MONOHYDRATE; SODIUM HYDROXYMETHYLGLYCINATE; SODIUM BENZOATE; ALOE VERA LEAF; WATER

Wipex MAX OUT! Value Sanitizing Wipes Refill Bag

Wipex MAX OUT! Value Sanitizing Wipes Refill Bag

Benzalkonium chloride 0.13%

Keep out of the reach of children. If swallowed, get medical help or contact a Poison Contrl right away.

Warnings

For external use only. Avoid cntact with the eyes. If in eyes, flush thoroughly with water.

Inactive Ingredients

Sodium benzoate, sodium chloride, citric acid, potassium sorbate, sodium hydroxymethylglycinate, aloe vera leaf, water

Purpose

Antiseptic

Stop Use

Stop and ask a doctor if:

Irritation or redness developes.

Conditions persists for more than 72 hours.

To Use

Sanitize hands or other affected area. Discard in trash after use.

To dispense

To begin: Break tab on bucket rim and pull off cover. Open bag inside to expose wipes, then thread center wipe through the lid. Replace bucket cover to maintain moisture.